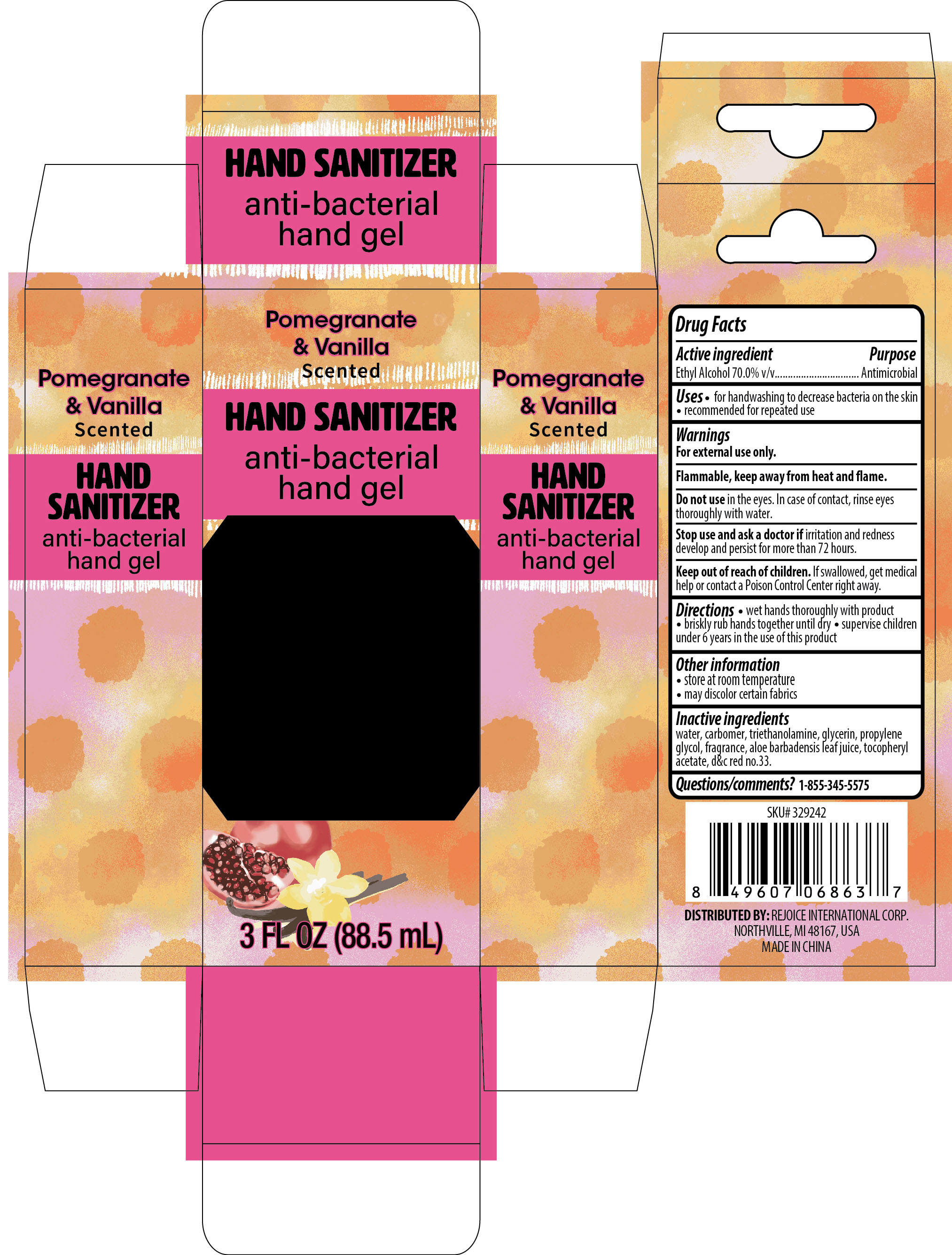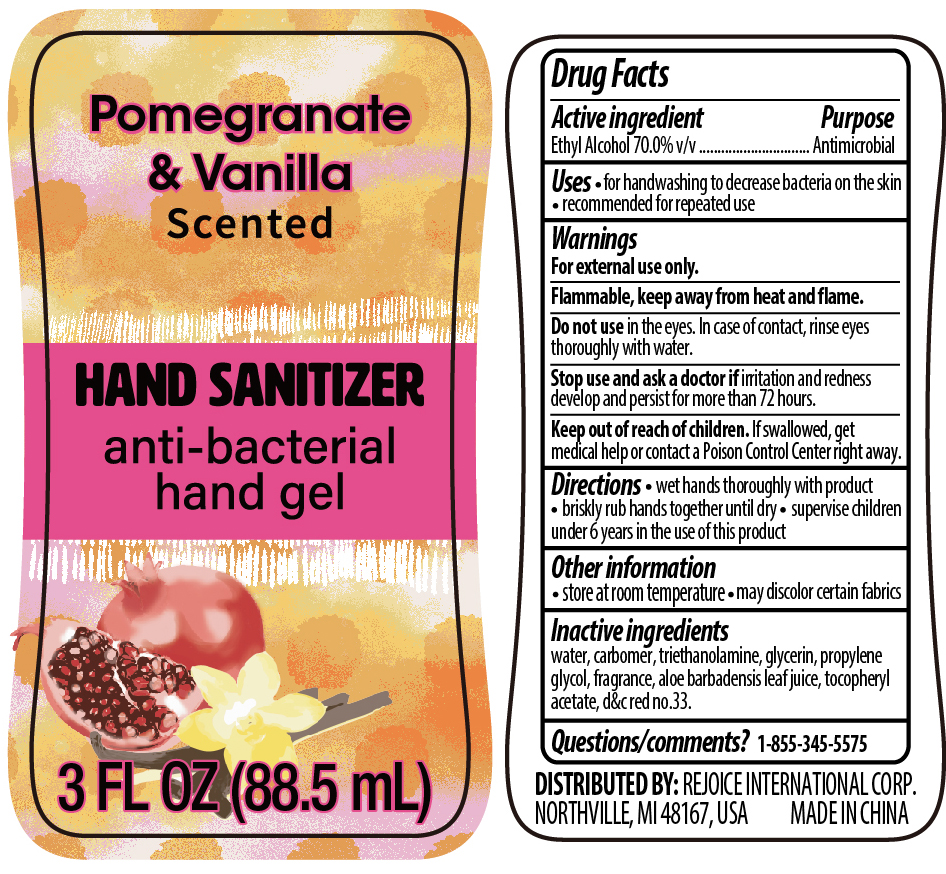 DRUG LABEL: Hand Sanitizer Pomegranate and Vanilla
NDC: 57337-137 | Form: LIQUID
Manufacturer: Ningbo Rejoice International
Category: otc | Type: HUMAN OTC DRUG LABEL
Date: 20250213

ACTIVE INGREDIENTS: ALCOHOL 70 mL/100 mL
INACTIVE INGREDIENTS: TROLAMINE; PROPYLENE GLYCOL; GLYCERIN; ALOE; CARBOMER HOMOPOLYMER, UNSPECIFIED TYPE; ALPHA-TOCOPHEROL ACETATE; D&C RED NO. 33; WATER

Hand Sanitizer 3oz Pomegranate & Vanilla

Active Ingredient(s)

Ethyl Alcohol 70% v/v.

Purpose

Antimicrobial

Use

- for handwashing to decrease bacteria on the skin
- recommended for repeated use

Warnings

For external use only. Flammable, keep away from heat or flame

Do not use

- in the eyes. In case of contact, rinse eyes thoroughly with water.

Stop use and ask a doctor if irritation or rednees develp and persist for more than 72 hours.

Keep out of reach of children. If swallowed, get medical help or contact a Poison Control Center right away.

Directions

- Wet hands thoroughly with product
- briskly rub hands together until dry.
- Supervise children under 6 years of age when using this product.

Other information

- Store at room temperature
- may discolor certain fabrics

Inactive ingredients

water, carbomer, triethanolamine, glycerin, propylene glycol, fragrance, aloe barbadensis leaf juice, tocopheryl acetate, d&c red no.33.

QUESTIONS

1-855-345-5575